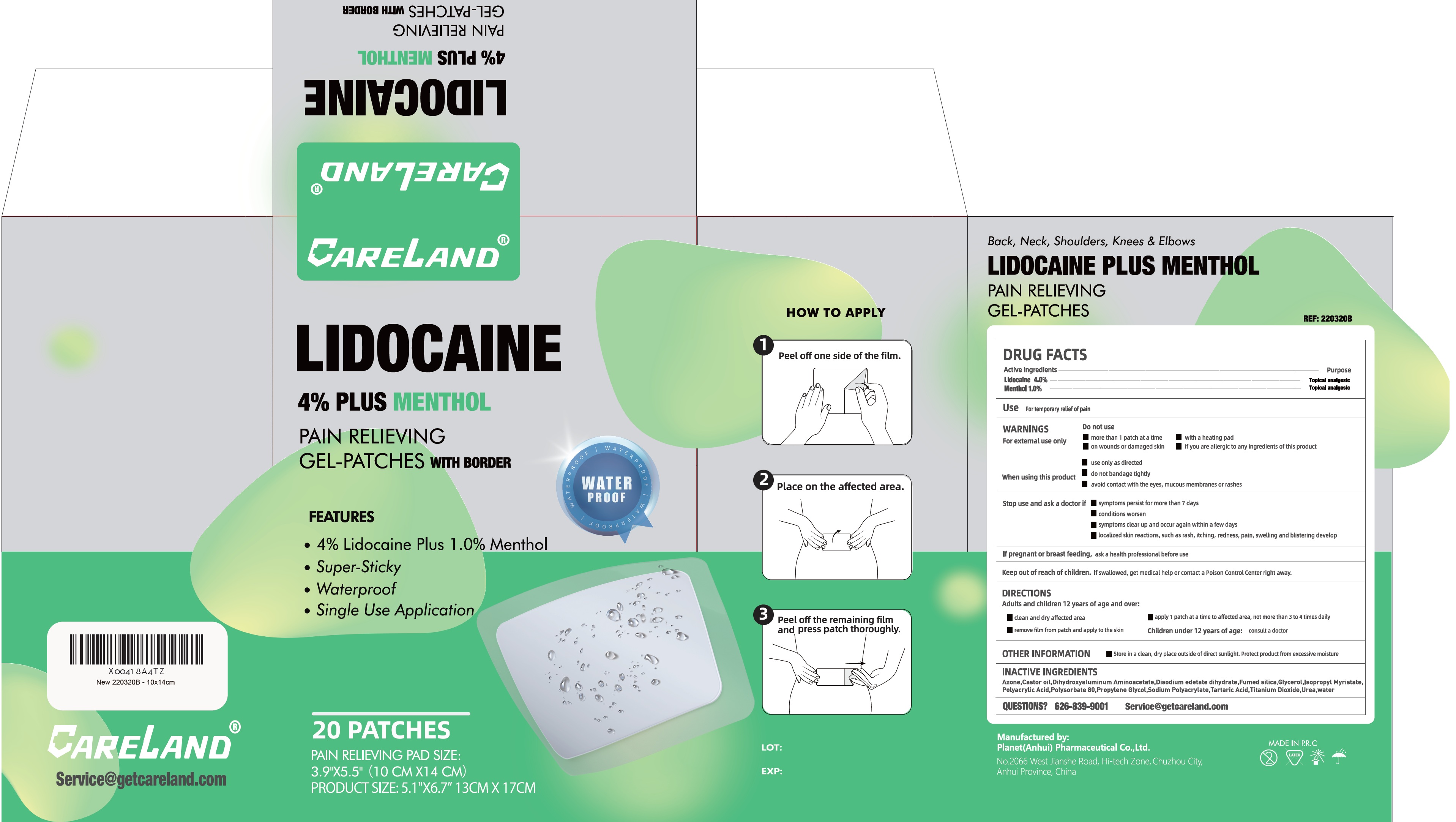 DRUG LABEL: Careland Lidocaine 4 Plus Menthol Pain Relieving Gel Patches for back, neck shoulders knees and elbows with border
NDC: 75568-014 | Form: PATCH
Manufacturer: Planet (Anhui) Pharmaceutical Co., Ltd.
Category: otc | Type: HUMAN OTC DRUG LABEL
Date: 20260212

ACTIVE INGREDIENTS: LIDOCAINE 40 mg/1 g; MENTHOL 10 mg/1 g
INACTIVE INGREDIENTS: LAUROCAPRAM; CASTOR OIL; DIHYDROXYALUMINUM AMINOACETATE; GLYCERIN; ISOPROPYL MYRISTATE; KAOLIN; POLYSORBATE 80; PROPYLENE GLYCOL; SORBITOL; TARTARIC ACID; TITANIUM DIOXIDE; WATER

Careland Lidocaine 4% Plus Menthol Pain Relieving Gel Patches for back, neck, shoulders, knees & elbows with border

Active ingredient

Lidocaine 4.0%

Menthol 1.0%

Purpose

Topical analgesic

Use

For temporary relief of pain

WARNINGS

For external use only

Do not use

- more than 1 patch at a time
- with a heating pad
- on wounds or damaged skin
- if you are allergic to any ingredients of this product

When using this product

- use only as directed
- do not bandage tightly
- avoid contact with the eyes, mucous membranes of rashes

Stop use and ask a doctor if

- symptoms persist for more than 7 days
- conditions worsen
- symptoms clear up and occur again within a few days
- localized skin reactions, such as rash, itching, redness, pain, swelling and blistering develop

If pregnant or breast feeding,

ask a health professional before use

Keep out of reach of children.

If swallowed, get medical help or contact a Poison Control Center right away.

DIRECTIONS

Adults and children 12 years of age and over:

- clean and dry affected area
- apply 1 patch at a time to affected area, not more than 3 to 4 times daily
- remove film from patch and apply to skin

Children under 12 years of age:consult a doctor

OTHER INFORMATION

- Store in a clean, dry place outside of direct sunlight. Protect product from excessive moisture

INACTIVE INGREDIENTS

Azone,Castor oil,CMC-Na,Dihydroxyaluminum Aminoacetate,Glycerol,Isopropyl Myristate,Kaolin,Polyacrylic Acid,Polysorbate 80, Propylene Glycol,Sorbitol,Sodium Polyacrylate,Tartaric Acid,Titanium Dioxide,Water

QUESTIONS?

1-888-655-1558 Service@getcareland.com